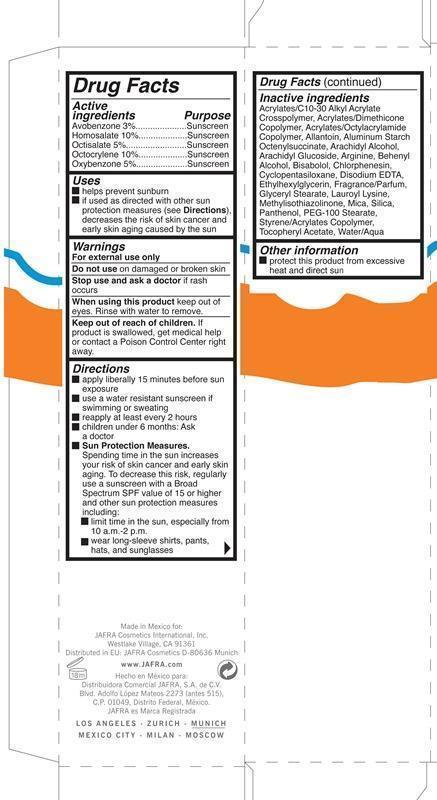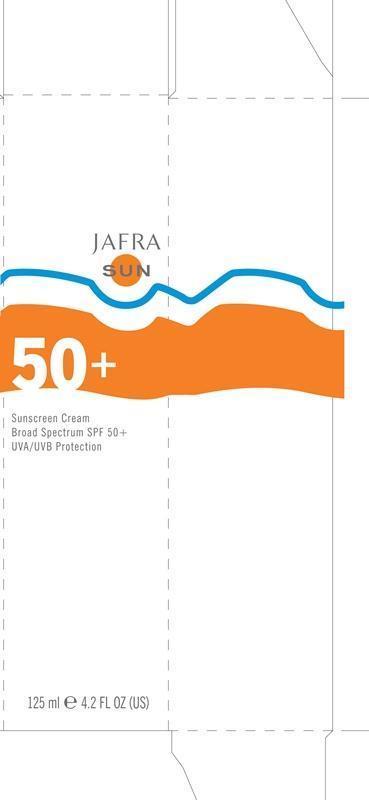 DRUG LABEL: Sunscreen Broad Spectrum SPF 50

NDC: 68828-165 | Form: CREAM
Manufacturer: JAFRA COSMETICS INTERNATIONAL
Category: otc | Type: HUMAN OTC DRUG LABEL
Date: 20200622

ACTIVE INGREDIENTS: AVOBENZONE 3 g/100 mL; HOMOSALATE 10 g/100 mL; OCTISALATE 5 g/100 mL; OCTOCRYLENE 10 g/100 mL; OXYBENZONE 5 g/100 mL
INACTIVE INGREDIENTS: CARBOMER INTERPOLYMER TYPE A (ALLYL SUCROSE CROSSLINKED); ALLANTOIN; ALUMINUM STARCH OCTENYLSUCCINATE; ARACHIDYL ALCOHOL; ARACHIDYL GLUCOSIDE; ARGININE; DOCOSANOL; LEVOMENOL; CHLORPHENESIN; CYCLOMETHICONE 5; EDETATE DISODIUM; ETHYLHEXYLGLYCERIN; GLYCERYL MONOSTEARATE; LAUROYL LYSINE; METHYLISOTHIAZOLINONE; MICA; SILICON DIOXIDE; PANTHENOL; PEG-100 STEARATE; .ALPHA.-TOCOPHEROL ACETATE; WATER

Sunscreen SPF 50

Active Ingredients Purpose

Avobenzone 3% Sunscreen

Homosalate 10% Sunscreen

Octisalate 5% Sunscreen

Octocrylene 10% Sunscreen

Oxybenzone 5% Sunscreen

Uses

helps prevent sunburn

if used as directed with other sun protection measures (see Directions), decreases the risk of skin cancer and early skin aging by the sun

Keep out of reach of children. If product is swallowed, get medical help or contact a Poison Control Center right away.

Stop use and ask a doctor if rash occurs

Warnings

For external use only

Do not use on on damaged or broken skin

When using this product keep out of eyes. Rinse with water to remove.

Directions

apply liberally 15 minutes before sun exposure

use a water resistant sunscreen if swimming or sweating

reapply at least ever 2 hours, especially if swimming, sweating, or after toweling

children under 6 months: Ask a doctor

Sun Protection Measures. Spending time in the sun increases your risk of skin cancer and early skin aging. To decrease this risk, regularly use a sunscreen with a Broad Spectrum SPF of 15 or higher and other sun protection measures including:

limit time in the sun, especially from 10 a.m.-2 p.m.

wear long-sleeve shirts, pants, hats, and sunglasses

INACTIVE INGREDIENT

Acrylates/C10-30 Alkyl Acrylate Crosspolymer, Acrylates/Dimethicone Copolymer, Acrylates/Octylacrylamide Copolymer, Allantoin, Aluminum Starch Octenylsuccinate, Arachidyl Alcohol, Arachidyl Glucoside, Arginine, Behenyl Alcohol, Bisabolol, Chlorphenesin, Cyclopentasiloxane, Disodium EDTA, Ethylhexylglycerin, Fragrance/parfum, Glyceryl Stearate, Lauroyl Lysine, Methylisothiazolinone, Mica, Silica, Panthenol, PEG-100 Stearate, Styrene/Acrylates Copolymer, Tocopheryl Acetate, Water/Aqua.

PACKAGE LABEL

Jafra Sun

50+

Sunscreen Cream Broad Spectrum SPF 50+

UVA/UVB Protection

125 ml 4.2 Fl Oz. (US)